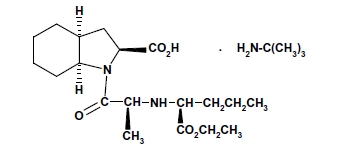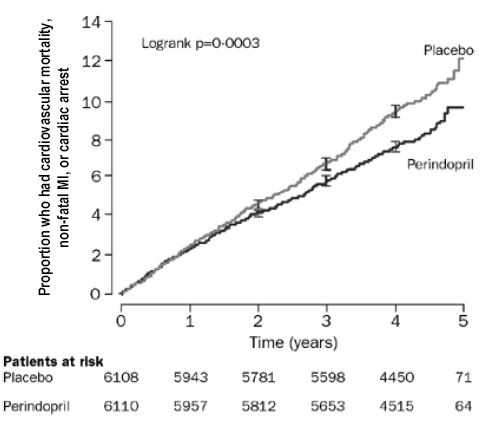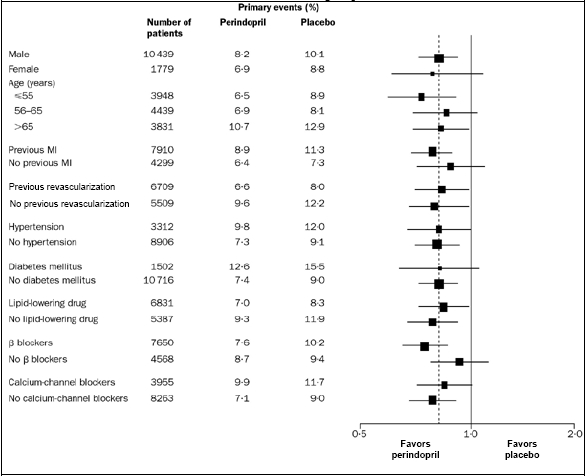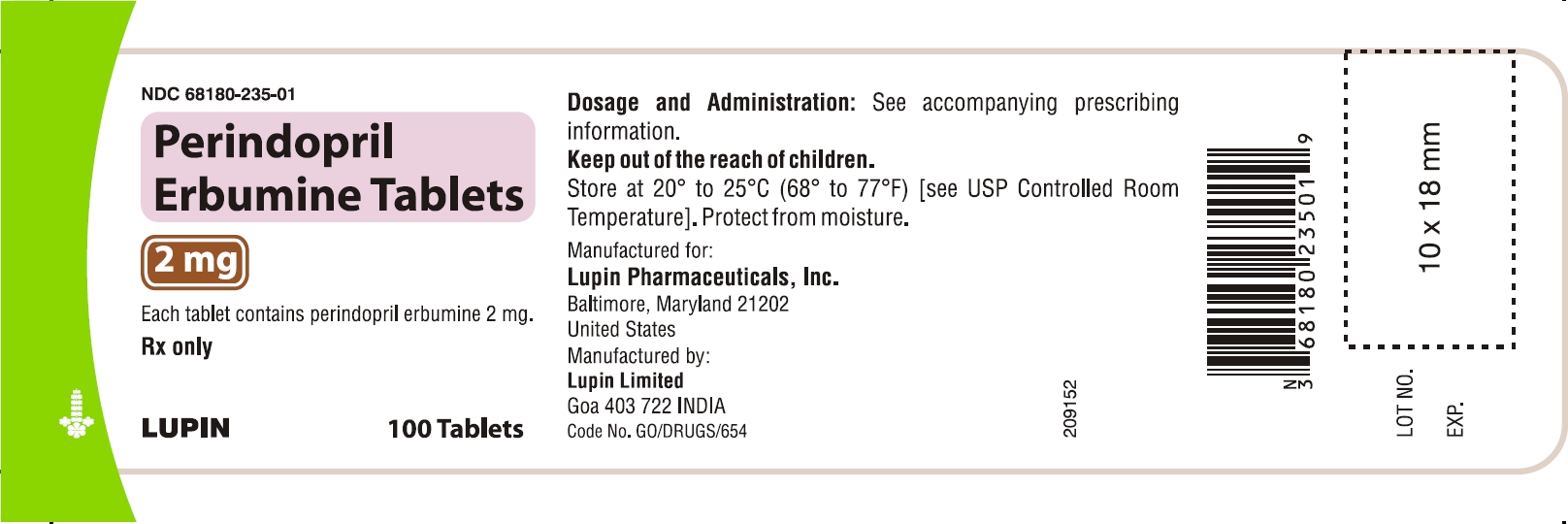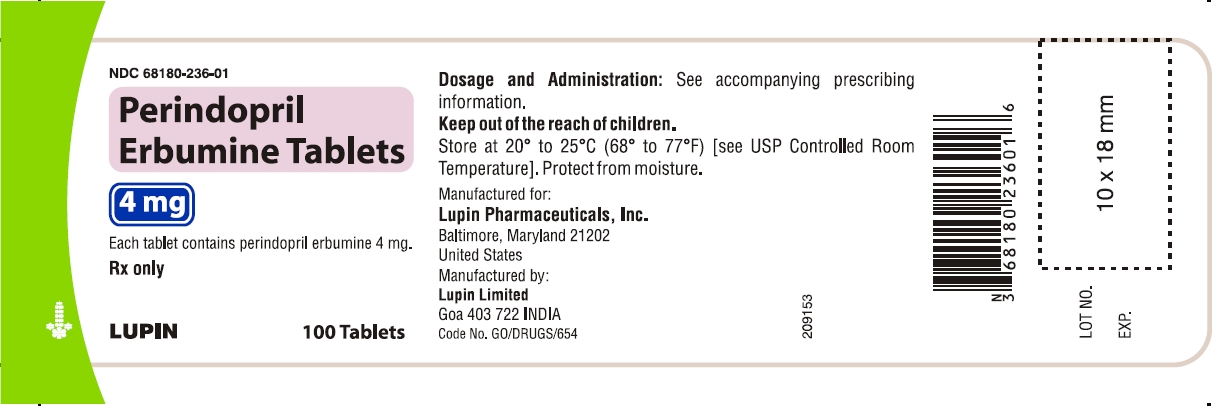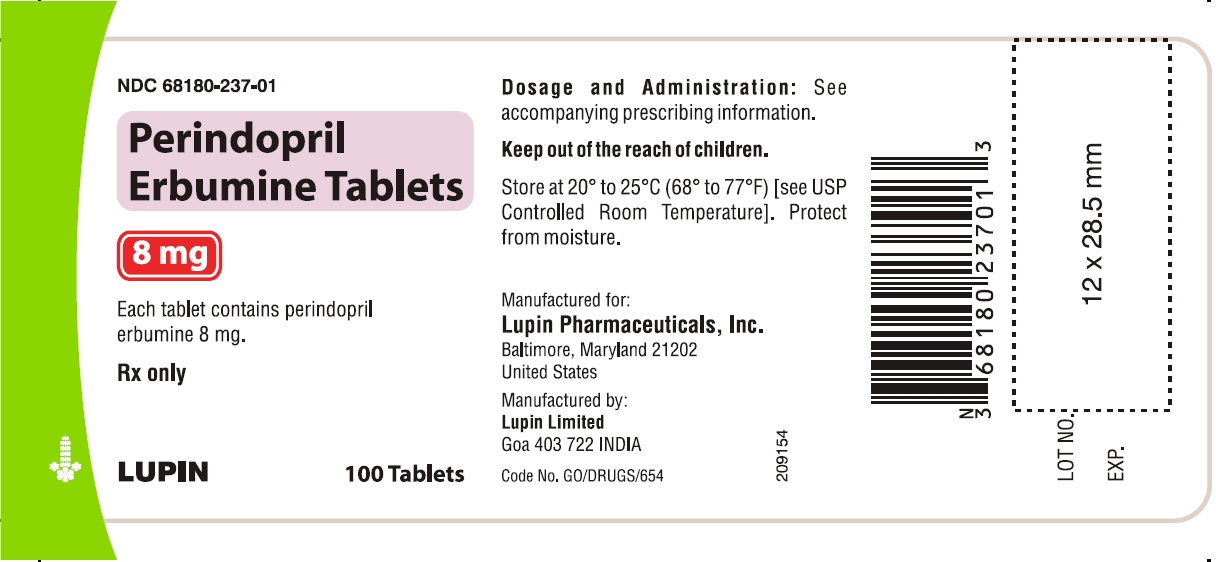 DRUG LABEL: Perindopril Erbumine
NDC: 68180-235 | Form: TABLET
Manufacturer: Lupin Pharmaceuticals, Inc
Category: prescription | Type: HUMAN PRESCRIPTION DRUG LABEL
Date: 20100101

ACTIVE INGREDIENTS: PERINDOPRIL ERBUMINE 2 mg/1 1
INACTIVE INGREDIENTS: SILICON DIOXIDE; LACTOSE MONOHYDRATE; MAGNESIUM STEARATE; CELLULOSE, MICROCRYSTALLINE

Perindopril Erbumine Tablets
2 mg, 4 mg and 8 mg

Rx only

USE IN PREGNANCY

When used in pregnancy, ACE inhibitors can cause injury and even death to the developing fetus. When pregnancy is detected, perindopril erbumine tablets should be discontinued as soon as possible. See WARNINGS: Fetal/Neonatal Morbidity and Mortality.

DESCRIPTION

Perindopril erbumine tablets are the tert-butylamine salt of perindopril, the ethyl ester of a non-sulfhydryl angiotensin-converting enzyme (ACE) inhibitor. Perindopril erbumine is chemically described as (2S,3αS,7αS)-1-[(S)-N-[(S)-1-Carboxy-butyl]alanyl]hexahydro-2-indolinecarboxylic acid, 1-ethyl ester, compound with tert-butylamine (1:1). Its molecular formula is C19H32N2O5C4H11N. Its structural formula is:

Perindopril erbumine is a white, crystalline powder with a molecular weight of 368.47 (free acid) or 441.61 (salt form). It is freely soluble in water (60% w/w), alcohol and chloroform.

Perindopril is the free acid form of perindopril erbumine, is a pro-drug and metabolized in vivo by hydrolysis of the ester group to form perindoprilat, the biologically active metabolite.

Perindopril erbumine tablets are available in 2 mg, 4 mg and 8 mg strengths for oral administration. In addition to perindopril erbumine, each tablet contains the following inactive ingredients: hydrophobic colloidal silica, lactose monohydrate, magnesium stearate and microcrystalline cellulose.

CLINICAL PHARMACOLOGY

Mechanism of Action:

Perindopril erbumine tablets are a pro-drug for perindoprilat, which inhibits ACE in human subjects and animals. The mechanism through which perindoprilat lowers blood pressure is believed to be primarily inhibition of ACE activity. ACE is a peptidyl dipeptidase that catalyzes conversion of the inactive decapeptide, angiotensin I, to the vasoconstrictor, angiotensin II. Angiotensin II is a potent peripheral vasoconstrictor, which stimulates aldosterone secretion by the adrenal cortex, and provides negative feedback on renin secretion. Inhibition of ACE results in decreased plasma angiotensin II, leading to decreased vasoconstriction, increased plasma renin activity and decreased aldosterone secretion. The latter results in diuresis and natriuresis and may be associated with a small increase of serum potassium.

ACE is identical to kininase II, an enzyme that degrades bradykinin. Whether increased levels of bradykinin, a potent vasodepressor peptide, play a role in the therapeutic effects of perindopril erbumine tablets remains to be elucidated.

While the principal mechanism of perindopril in blood pressure reduction is believed to be through the renin-angiotensin-aldosterone system, ACE inhibitors have some effect even in apparent low-renin hypertension. Perindopril has been studied in relatively few black patients, usually a low-renin population, and the average response of diastolic blood pressure to perindopril was about half the response seen in nonblacks, a finding consistent with previous experience of other ACE inhibitors.

After administration of perindopril, ACE is inhibited in a dose and blood concentration-related fashion, with the maximal inhibition of 80 to 90% attained by 8 mg persisting for 10 to 12 hours. Twenty-four hour ACE inhibition is about 60% after these doses. The degree of ACE inhibition achieved by a given dose appears to diminish over time (the ID50 increases). The pressor response to an angiotensin I infusion is reduced by perindopril, but this effect is not as persistent as the effect on ACE; there is about 35% inhibition at 24 hours after a 12 mg dose.

Pharmacokinetics:

Oral administration of perindopril erbumine tablets results in its rapid absorption with peak plasma concentrations occurring at approximately 1 hour. The absolute oral bioavailability of perindopril is about 75%. Following absorption, approximately 30 to 50% of systemically available perindopril is hydrolyzed to its active metabolite, perindoprilat, which has a mean bioavailability of about 25%. Peak plasma concentrations of perindoprilat are attained 3 to 7 hours after perindopril administration. The presence of food in the gastrointestinal tract does not affect the rate or extent of absorption of perindopril but reduces bioavailability of perindoprilat by about 35%. (See PRECAUTIONS: Food Interaction.)

With 4, 8 and 16 mg doses of perindopril erbumine tablets, Cmax and AUC of perindopril and perindoprilat increase in a linear and dose-proportional manner following both single oral dosing and at steady state during a once-a-day multiple dosing regimen.

Perindopril exhibits multiexponential pharmacokinetics following oral administration. The mean half-life of perindopril associated with most of its elimination is approximately 0.8 to 1.0 hours. At very low plasma concentrations of perindopril (<3 ng/mL), there is a prolonged terminal elimination half-life, similar to that seen with other ACE inhibitors, that results from slow dissociation of perindopril from plasma/tissue ACE binding sites. Perindopril does not accumulate with a once-a-day multiple dosing regimen. Mean total body clearance of perindopril is 219 to 362 mL/min and its mean renal clearance is 23.3 to 28.6 mL/min.

Perindopril is extensively metabolized following oral administration, with only 4 to 12% of the dose recovered unchanged in the urine. Six metabolites resulting from hydrolysis, glucuronidation and cyclization via dehydration have been identified. These include the active ACE inhibitor, perindoprilat (hydrolyzed perindopril), perindopril and perindoprilat glucuronides, dehydrated perindopril and the diastereoisomers of dehydrated perindoprilat. In humans, hepatic esterase appears to be responsible for the hydrolysis of perindopril.

The active metabolite, perindoprilat, also exhibits multiexponential pharmacokinetics following the oral administration of perindopril erbumine tablets. Formation of perindoprilat is gradual with peak plasma concentrations occurring between 3 and 7 hours. The subsequent decline in plasma concentration shows an apparent mean half-life of 3 to 10 hours for the majority of the elimination, with a prolonged terminal elimination half-life of 30 to 120 hours resulting from slow dissociation of perindoprilat from plasma/tissue ACE binding sites. During repeated oral once-daily dosing with perindopril, perindoprilat accumulates about 1.5 to 2.0 fold and attains steady state plasma levels in 3 to 6 days. The clearance of perindoprilat and its metabolites is almost exclusively renal.

Approximately 60% of circulating perindopril is bound to plasma proteins, and only 10 to 20% of perindoprilat is bound. Therefore, drug interactions mediated through effects on protein binding are not anticipated.

At usual antihypertensive dosages, little radioactivity (<5% of the dose) was distributed to the brain after administration of 14C-perindopril to rats.

Radioactivity was detectable in fetuses and in milk after administration of 14C-perindopril to pregnant and lactating rats.

Elderly Patients: Plasma concentrations of both perindopril and perindoprilat in elderly patients (>70 yrs) are approximately twice those observed in younger patients, reflecting both increased conversion of perindopril to perindoprilat and decreased renal excretion of perindoprilat. (See PRECAUTIONS: Geriatric Use.)

Heart Failure Patients: Perindoprilat clearance is reduced in congestive heart failure patients, resulting in a 40% higher dose interval AUC. (See DOSAGE AND ADMINISTRATION.)

Patients with Renal Insufficiency: With perindopril erbumine doses of 2 to 4 mg, perindoprilat AUC increases with decreasing renal function. At creatinine clearances of 30 to 80 mL/min, AUC is about double that of 100 mL/min. When creatinine clearance drops below 30 mL/min, AUC increases more markedly.

In a limited number of patients studied, perindopril dialysis clearance ranged from 41.7 to 76.7 mL/min (mean 52.0 mL/min). Perindoprilat dialysis clearance ranged from 37.4 to 91.0 mL/min (mean 67.2 mL/min). (See DOSAGE AND ADMINISTRATION.)

Patients with Hepatic Insufficiency: The bioavailability of perindoprilat is increased in patients with impaired hepatic function. Plasma concentrations of perindoprilat in patients with impaired liver function were about 50% higher than those observed in healthy subjects or hypertensive patients with normal liver function.

Pharmacodynamics and Clinical Effects:

Stable Coronary Artery Disease

The EURopean trial On reduction of cardiac events with Perindopril in stable coronary Artery disease (EUROPA) was a multicenter, randomized, double-blind and placebo-controlled study conducted in 12,218 patients who had evidence of stable coronary artery disease without clinical heart failure. Patients had evidence of coronary artery disease documented by previous myocardial infarction more than 3 months before screening, coronary revascularization more than 6 months before screening, angiographic evidence of stenosis (at least 70% narrowing of one or more major coronary arteries), or positive stress test in men with a history of chest pain. After a run-in period of 4 weeks during which all patients received perindopril 2 mg to 8 mg, the patients were randomly assigned to perindopril 8 mg once daily (n=6,110) or matching placebo (n=6,108). The mean follow-up was 4.2 years. The study examined the long-term effects of perindopril on time to first event of cardiovascular mortality, nonfatal myocardial infarction, or cardiac arrest in patients with stable coronary artery disease.

The mean age of patients was 60 years; 85% were male, 92% were taking platelet inhibitors, 63% were taking β blockers, and 56% were taking lipid-lowering therapy. The EUROPA study showed that perindopril significantly reduced the relative risk for the primary endpoint events (Table 1). This beneficial effect is largely attributable to a reduction in the risk of non-fatal myocardial infarction. This beneficial effect of perindopril on the primary outcome was evident after about one year of treatment (Figure 1).

Table 1. Primary Endpoint and Relative Risk Reduction
 | Perindopril; (N = 6,110) | Placebo; (N = 6,108) | RRR; (95% CI) | P
Combined Endpoint; Cardiovascular mortality, non-fatal MI or cardiac arrest | 488 (8.0%) | 603 (9.9%) | 20% (9 to 29) | 0.0003
Component Endpoint; Cardiovascular mortality; Non-fatal MI; Cardiac arrest | 215 (3.5%); 295 (4.8%); 6 (0.1%) | 249 (4.1%); 378 (6.2%); 11 (0.2%) | 14% (-3 to 28); 22% (10 to 33); 46% (-47 to 80) | 0.107; 0.001; 0.22
RRR: relative risk reduction; MI: myocardial infarction

The outcome was similar across all predefined subgroups by age, underlying disease or concomitant medication (Figure 2).

Figure 1. Time to First Occurrence of Primary Endpoint

Figure 2. Beneficial Effect of Perindopril Treatment on Primary Endpoint in Predefined Subgroups

Size of squares proportional to the number of patients in that group. Dashed line indicates overall relative risk.

Hypertension

In placebo-controlled studies of perindopril monotherapy (2 to 16 mg q.d.) in patients with a mean blood pressure of about 150/100 mm Hg, 2 mg had little effect, but doses of 4 to 16 mg lowered blood pressure. The 8 and 16 mg doses were indistinguishable, and both had a greater effect than the 4 mg dose. The magnitude of the blood pressure effect was similar in the standing and supine positions, generally about 1 mm Hg greater on standing. In these studies, doses of 8 and 16 mg per day gave supine, trough blood pressure reductions of 9 to 15/5 to 6 mm Hg. When once-daily and twice-daily dosing were compared, the B.I.D. regimen was generally slightly superior, but by not more than about 0.5 to 1 mm Hg. After 2 to 16 mg doses of perindopril, the trough mean systolic and diastolic blood pressure effects were approximately equal to the peak effects (measured 3 to 7 hours after dosing.). Trough effects were about 75 to 100% of peak effects. When perindopril was given to patients receiving 25 mg HCTZ, it had an added effect similar in magnitude to its effect as monotherapy, but 2 to 8 mg doses were approximately equal in effectiveness. In general, the effect of perindopril occurred promptly, with effects increasing slightly over several weeks.

In hemodynamic studies carried out in animal models of hypertension, blood pressure reduction after perindopril administration was accompanied by a reduction in peripheral arterial resistance and improved arterial wall compliance. In studies carried out in patients with essential hypertension, the reduction in blood pressure was accompanied by a reduction in peripheral resistance with no significant changes in heart rate or glomerular filtration rate. An increase in the compliance of large arteries was also observed, suggesting a direct effect on arterial smooth muscle, consistent with the results of animal studies.

Formal interaction studies of perindopril erbumine tablets have not been carried out with antihypertensive agents other than thiazides. Limited experience in controlled and uncontrolled trials coadministering perindopril erbumine tablets with a calcium channel blocker, a loop diuretic or triple therapy (beta-blocker, vasodilator and a diuretic), does not suggest any unexpected interactions. In general, ACE inhibitors have less than additive effects when given with beta-adrenergic blockers, presumably because both work in part through the renin angiotensin system. A controlled pharmacokinetic study has shown no effect on plasma digoxin concentrations when coadministered with perindopril erbumine tablets. (See PRECAUTIONS: Drug Interactions.)

In uncontrolled studies in patients with insulin-dependent diabetes, perindopril did not appear to affect glycemic control. In long-term use, no effect on urinary protein excretion was seen in these patients.

The effectiveness of perindopril erbumine tablets was not influenced by sex and it was less effective in blacks than in nonblacks. In elderly patients (≥60 years), the mean blood pressure effect was somewhat smaller than in younger patients, although the difference was not significant.

INDICATIONS AND USAGE

Stable Coronary Artery Disease

Perindopril erbumine tablets are indicated in patients with stable coronary artery disease to reduce the risk of cardiovascular mortality or non-fatal myocardial infarction. Perindopril erbumine tablets can be used with conventional treatment for management of coronary artery disease, such as antiplatelet, antihypertensive or lipid-lowering therapy.

Hypertension

Perindopril erbumine tablets are indicated for the treatment of patients with essential hypertension. Perindopril erbumine tablets may be used alone or given with other classes of antihypertensives, especially thiazide diuretics.

When using perindopril erbumine tablets, consideration should be given to the fact that another angiotensin converting enzyme inhibitor (captopril) has caused agranulocytosis, particularly in patients with renal impairment or collagen vascular disease. Available data are insufficient to determine whether perindopril erbumine tablets has a similar potential. (See WARNINGS.)

In considering use of perindopril erbumine tablets, it should be noted that in controlled trials ACE inhibitors have an effect on blood pressure that is less in black patients than in nonblacks. In addition, it should be noted that black patients receiving ACE inhibitor monotherapy have been reported to have a higher incidence of angioedema compared to nonblacks. (See WARNINGS: Head and Neck Angioedema.)

CONTRAINDICATIONS

Perindopril erbumine tablets are contraindicated in patients known to be hypersensitive to this product or to any other ACE inhibitor. Perindopril erbumine tablets are also contraindicated in patients with a history of angioedema related to previous treatment with an ACE inhibitor.

WARNINGS

Anaphylactoid and Possibly Related Reactions:

Presumably because angiotensin-converting enzyme inhibitors affect the metabolism of eicosanoids and polypeptides, including endogenous bradykinin, patients receiving ACE inhibitors (including perindopril erbumine tablets) may be subject to a variety of adverse reactions, some of them serious.

Head and Neck Angioedema:

Angioedema involving the face, extremities, lips, tongue, glottis and/or larynx has been reported in patients treated with ACE inhibitors, including perindopril erbumine tablets (0.1% of patients treated with perindopril erbumine tablets in U.S. clinical trials). In such cases, perindopril erbumine tablets should be promptly discontinued and the patient carefully observed until the swelling disappears. In instances where swelling has been confined to the face and lips, the condition has generally resolved without treatment, although antihistamines have been useful in relieving symptoms. Angioedema associated with involvement of the tongue, glottis or larynx may be fatal due to airway obstruction. Appropriate therapy, such as subcutaneous epinephrine solution 1:1000 (0.3 to 0.5 mL), should be promptly administered. Patients with a history of angioedema unrelated to ACE inhibitor therapy may be at increased risk of angioedema while receiving an ACE inhibitor.

Intestinal Angioedema:

Intestinal angioedema has been reported in patients treated with ACE inhibitors. These patients presented with abdominal pain (with or without nausea or vomiting); in some cases there was no prior history of facial angioedema and C-1 esterase levels were normal. The angioedema was diagnosed by procedures including abdominal CT scan or ultrasound, or at surgery, and symptoms resolved after stopping the ACE inhibitor. Intestinal angioedema should be included in the differential diagnosis of patients on ACE inhibitors presenting with abdominal pain.

Anaphylactoid Reactions During Desensitization:

Two patients undergoing desensitizing treatment with hymenoptera venom while receiving ACE inhibitors sustained life-threatening anaphylactoid reactions. In the same patients, these reactions were avoided when ACE inhibitors were temporarily withheld, but they reappeared upon inadvertent rechallenge.

Anaphylactoid Reactions During Membrane Exposure:

Anaphylactoid reactions have been reported in patients dialyzed with high-flux membranes and treated concomitantly with an ACE inhibitor. Anaphylactoid reactions have also been reported in patients undergoing low-density lipoprotein apheresis with dextran sulfate absorption.

Hypotension:

Like other ACE inhibitors, perindopril erbumine tablets can cause symptomatic hypotension. Perindopril erbumine tablets have been associated with hypotension in 0.3% of uncomplicated hypertensive patients in U.S. placebo-controlled trials. Symptoms related to orthostatic hypotension were reported in another 0.8% of patients.

Symptomatic hypotension associated with the use of ACE inhibitors is more likely to occur in patients who have been volume and/or salt-depleted, as a result of prolonged diuretic therapy, dietary salt restriction, dialysis, diarrhea or vomiting. Volume and/or salt depletion should be corrected before initiating therapy with perindopril erbumine tablets. (See DOSAGE AND ADMINISTRATION.)

In patients with congestive heart failure, with or without associated renal insufficiency, ACE inhibitors may cause excessive hypotension, and may be associated with oliguria or azotemia, and rarely with acute renal failure and death. In patients with ischemic heart disease or cerebrovascular disease such an excessive fall in blood pressure could result in a myocardial infarction or a cerebrovascular accident.

In patients at risk of excessive hypotension, perindopril erbumine tablets therapy should be started under very close medical supervision. Patients should be followed closely for the first two weeks of treatment and whenever the dose of perindopril erbumine tablets and/or diuretic is increased.

If excessive hypotension occurs, the patient should be placed immediately in a supine position and, if necessary, treated with an intravenous infusion of physiological saline. Perindopril erbumine tablets treatment can usually be continued following restoration of volume and blood pressure.

Neutropenia/Agranulocytosis:

Another ACE inhibitor, captopril, has been shown to cause agranulocytosis and bone marrow depression, rarely in uncomplicated patients but more frequently in patients with renal impairment, especially patients with a collagen vascular disease such as systemic lupus erythematosus or scleroderma. Available data from clinical trials of perindopril erbumine tablets are insufficient to show whether perindopril erbumine tablets causes agranulocytosis at similar rates.

Fetal/Neonatal Morbidity and Mortality:

ACE inhibitors can cause fetal and neonatal morbidity and death when administered to pregnant women. Several dozen cases have been reported in the world literature. When pregnancy is detected, ACE inhibitors should be discontinued as soon as possible.

The use of ACE inhibitors during the second and third trimesters of pregnancy has been associated with fetal and neonatal injury, including hypotension, neonatal skull hypoplasia, anuria, reversible or irreversible renal failure and death. Oligohydramnios has also been reported, presumably resulting from decreased fetal renal function; oligohydramnios in this setting has been associated with fetal limb contractures, craniofacial deformation and hypoplastic lung development.

Prematurity, intrauterine growth retardation, patent ductus arteriosus, and other structural cardiac malformations, as well as neurological malformations, have been reported following exposure to ACE inhibitors during the first trimester of pregnancy.

When patients become pregnant, physicians should make every effort to discontinue the use of perindopril erbumine tablets as soon as possible. Rarely (probably less often than once in every thousand pregnancies), no alternative to ACE inhibitors will be found. In these rare cases, the mothers should be apprised of the potential hazards to their fetuses, and serial ultrasound examinations should be performed to assess the intra-amniotic environment.

If oligohydramnios is observed, perindopril erbumine tablets should be discontinued unless it is considered life-saving for the mother. Contraction stress testing (CST), a non-stress test (NST) or biophysical profiling (BPP) may be appropriate, depending upon the week of pregnancy. Patients and physicians should be aware, however, that oligohydramnios may not appear until after the fetus has sustained irreversible injury.

Infants with histories of in utero exposure to ACE inhibitors should be closely observed for hypotension, oliguria and hyperkalemia. If oliguria occurs, attention should be directed toward support of blood pressure and renal perfusion. Exchange transfusion or dialysis may be required as means of reversing hypotension and/or substituting for disordered renal function. Perindopril, which crosses the placenta, can theoretically be removed from the neonatal circulation by these means, but limited experience has not shown that such removal is central to the treatment of these infants.

No teratogenic effects of perindopril were seen in studies of pregnant rats, mice, rabbits and cynomolgus monkeys. On a mg/m^2 basis, the doses used in these studies were 6 times (in mice), 670 times (in rats), 50 times (in rabbits) and 17 times (in monkeys) the maximum recommended human dose (assuming a 50 kg adult). On a mg/kg basis, these multiples are 60 times (in mice), 3,750 times (in rats), 150 times (in rabbits) and 50 times (in monkeys) the maximum recommended human dose.

Hepatic Failure:

Rarely, ACE inhibitors have been associated with a syndrome that starts with cholestatic jaundice and progresses to fulminant hepatic necrosis and (sometimes) death. The mechanism of this syndrome is not understood. Patients receiving ACE inhibitors who develop jaundice or marked elevations of hepatic enzymes should discontinue the ACE inhibitor and receive appropriate medical follow-up.

PRECAUTIONS

General:

Impaired Renal Function: As a consequence of inhibiting the renin-angiotensin-aldosterone system, changes in renal function may be anticipated in susceptible individuals.

Hypertensive Patients with Congestive Heart Failure: In patients with severe congestive heart failure, where renal function may depend on the activity of the renin-angiotensin-aldosterone system, treatment with ACE inhibitors, including perindopril erbumine tablets, may be associated with oliguria and/or progressive azotemia, and rarely with acute renal failure and/or death.

Hypertensive Patients with Renal Artery Stenosis: In hypertensive patients with unilateral or bilateral renal artery stenosis, increases in blood urea nitrogen and serum creatinine may occur. Experience with ACE inhibitors suggests that these increases are usually reversible upon discontinuation of the drug. In such patients, renal function should be monitored during the first few weeks of therapy.

Some hypertensive patients without apparent pre-existing renal vascular disease have developed increases in blood urea nitrogen and serum creatinine, usually minor and transient. These increases are more likely to occur in patients treated concomitantly with a diuretic and in patients with pre-existing renal impairment. Reduction of dosages of perindopril erbumine tablets, the diuretic or both may be required. In some cases, discontinuation of either or both drugs may be necessary.

Evaluation of hypertensive patients should always include an assessment of renal function. (See DOSAGE AND ADMINISTRATION.)

Hyperkalemia: Elevations of serum potassium have been observed in some patients treated with ACE inhibitors, including perindopril erbumine tablets. In U.S. controlled clinical trials, 1.4% of the patients receiving perindopril erbumine tablets and 2.3% of patients receiving placebo showed increased serum potassium levels to greater than 5.7 mEq/L. Most cases were isolated single values that did not appear clinically relevant and were rarely a cause for withdrawal. Risk factors for the development of hyperkalemia include renal insufficiency, diabetes mellitus and the concomitant use of agents such as potassium-sparing diuretics, potassium supplements and/or potassium-containing salt substitutes. Drugs associated with increases in serum potassium should be used cautiously, if at all, with perindopril erbumine tablets. (See PRECAUTIONS: Drug Interactions.)

Cough: Presumably due to the inhibition of the degradation of endogenous bradykinin, persistent nonproductive cough has been reported with all ACE inhibitors, always resolving after discontinuation of therapy. ACE inhibitor-induced cough should be considered in the differential diagnosis of cough. In controlled trials with perindopril, cough was present in 12% of perindopril patients and 4.5% of patients given placebo.

Surgery/Anesthesia: In patients undergoing surgery or during anesthesia with agents that produce hypotension, perindopril erbumine tablets may block angiotensin II formation that would otherwise occur secondary to compensatory renin release. Hypotension attributable to this mechanism can be corrected by volume expansion.

Information for Patients:

Angioedema: Angioedema, including laryngeal edema, can occur with ACE inhibitor therapy, especially following the first dose. Patients should be told to report immediately signs or symptoms suggesting angioedema (swelling of face, extremities, eyes, lips, tongue, hoarseness or difficulty in swallowing or breathing) and to take no more drug before consulting a physician.

Symptomatic Hypotension: As with any antihypertensive therapy, patients should be cautioned that lightheadedness can occur, especially during the first few days of therapy and that it should be reported promptly. Patients should be told that if fainting occurs, perindopril erbumine tablets should be discontinued and a physician consulted.

All patients should be cautioned that inadequate fluid intake or excessive perspiration, diarrhea or vomiting can lead to an excessive fall in blood pressure in association with ACE inhibitor therapy.

Hyperkalemia: Patients should be advised not to use potassium supplements or salt substitutes containing potassium without a physician’s advice.

Neutropenia: Patients should be told to report promptly any indication of infection (e.g., sore throat, fever), which could be a sign of neutropenia.

Pregnancy: Female patients of childbearing age should be told about the consequences of exposure to ACE inhibitors during pregnancy. Discuss other treatment options with women planning to become pregnant. Women who do become pregnant while on an ACE inhibitor (including perindopril erbumine) should be asked to stop the medication and contact their physician as soon as possible.

Drug Interactions:

Diuretics: Patients on diuretics, and especially those started recently, may occasionally experience an excessive reduction of blood pressure after initiation of perindopril erbumine tablets therapy. The possibility of hypotensive effects can be minimized by either discontinuing the diuretic or increasing the salt intake prior to initiation of treatment with perindopril. If diuretics cannot be interrupted, close medical supervision should be provided with the first dose of perindopril erbumine tablets, for at least two hours and until blood pressure has stabilized for another hour. (See WARNINGS and DOSAGE AND ADMINISTRATION.)

The rate and extent of perindopril absorption and elimination are not affected by concomitant diuretics. The bioavailability of perindoprilat was reduced by diuretics, however, and this was associated with a decrease in plasma ACE inhibition.

Potassium Supplements and Potassium-Sparing Diuretics: Perindopril erbumine tablets may increase serum potassium because of its potential to decrease aldosterone production. Use of potassium-sparing diuretics (spironolactone, amiloride, triamterene and others), potassium supplements or other drugs capable of increasing serum potassium (indomethacin, heparin, cyclosporine and others) can increase the risk of hyperkalemia. Therefore, if concomitant use of such agents is indicated, they should be given with caution and the patient’s serum potassium should be monitored frequently.

Lithium: Increased serum lithium and symptoms of lithium toxicity have been reported in patients receiving concomitant lithium and ACE inhibitor therapy. These drugs should be coadministered with caution and frequent monitoring of serum lithium concentration is recommended. Use of a diuretic may further increase the risk of lithium toxicity.

Gold: Nitritoid reactions (symptoms include facial flushing, nausea, vomiting, and hypotension) have been reported rarely in patients on therapy with injectable gold (sodium aurothiomalate) and concomitant ACE Inhibitor therapy including perindropil erbumine tablets.

Digoxin: A controlled pharmacokinetic study has shown no effect on plasma digoxin concentrations when co-administered with perindopril erbumine tablets, but an effect of digoxin on the plasma concentration of perindopril/perindoprilat has not been excluded.

Gentamicin: Animal data have suggested the possibility of interaction between perindopril and gentamicin. However, this has not been investigated in human studies. Co-administration of both drugs should proceed with caution.

Food Interaction: Oral administration of perindopril erbumine tablets with food does not significantly lower the rate or extent of perindopril absorption relative to the fasted state. However, the extent of biotransformation of perindopril to the active metabolite, perindoprilat, is reduced approximately 43%, resulting in a reduction in the plasma ACE inhibition curve of approximately 20%, probably clinically insignificant. In clinical trials, perindopril was generally administered in a non-fasting state.

Carcinogenesis, Mutagenesis, Impairment of Fertility:

Carcinogenesis: No evidence of carcinogenic effect was observed in studies in rats and mice when perindopril was administered at dosages up to 20 times (mg/kg) or 2 to 4 times (mg/m^2) the maximum proposed clinical doses (16 mg/day) for 104 weeks.

Mutagenesis: No genotoxic potential was detected for perindopril erbumine tablets, perindoprilat and other metabolites in various in vitro and in vivo investigations, including the Ames test, the Saccharomyces cerevisiae D4 test, cultured human lymphocytes, TK ± mouse lymphoma assay, mouse and rat micronucleus tests and Chinese hamster bone marrow assay.

Impairment of Fertility: There was no meaningful effect on reproductive performance or fertility in the rat given up to 30 times (mg/kg) or 6 times (mg/m^2) the proposed maximum clinical dosage of perindopril erbumine tablets during the period of spermatogenesis in males or oogenesis and gestation in females.

Pregnancy:

Pregnancy Categories D. (See WARNINGS: Fetal/Neonatal Morbidity and Mortality.)

Nursing Mothers:

Milk of lactating rats contained radioactivity following administration ^14C-perindopril. It is not known whether perindopril is secreted in human milk. Because many drugs are secreted in human milk, caution should be exercised when perindopril erbumine tablets are given to nursing mothers.

Pediatric Use:

Safety and effectiveness of perindopril erbumine tablets in pediatric patients have not been established.

Geriatric Use:

The mean blood pressure effect of perindopril was somewhat smaller in patients over 60 than in younger patients, although the difference was not significant. Plasma concentrations of both perindopril and perindoprilat were increased in elderly patients compared to concentrations in younger patients. No adverse effects were clearly increased in older patients with the exception of dizziness and possibly rash.

Perindopril should be used with caution when administered to elderly patients who are at an increased risk for falls due to age, their underlying disease and/or their concurrent use of medications(s) associated with falls. Falls and fall-related events may be exacerbated by the central nervous system effects of dizziness and syncope as well as the symptomatic hypotension, including orthostatic, associated with perindopril. Experience with perindopril erbumine tablets in elderly patients at daily doses exceeding 8 mg is limited.

ADVERSE REACTIONS

Hypertension

Perindopril erbumine tablets have been evaluated for safety in approximately 3,400 patients with hypertension in U.S. and foreign clinical trials. Perindopril erbumine tablets were in general well tolerated in the patient populations studied, the side effects were usually mild and transient. Although dizziness was reported more frequently in placebo patients (8.5%) than in perindopril patients (8.2%), the incidence appeared to increase with an increase in perindopril dose.

The data presented here are based on results from the 1,417 perindopril erbumine tablets -treated patients who participated in the U.S. clinical trials. Over 220 of these patients were treated with perindopril erbumine tablets for at least one year.

In placebo-controlled U.S. clinical trials, the incidence of premature discontinuation of therapy due to adverse events was 6.5% in patients treated with perindopril erbumine tablets and 6.7% in patients treated with placebo. The most common causes were cough, headache, asthenia and dizziness.

Among 1,012 patients in placebo-controlled U.S. trials, the overall frequency of reported adverse events was similar in patients treated with perindopril erbumine tablets and in those treated with placebo (approximately 75% in each group). Adverse events that occurred in 1% or greater of the patients and that were more common for perindopril than placebo by at least 1% (regardless of whether they were felt to be related to study drug) are shown in the first two columns below. Of these adverse events, those considered possibly or probably related to study drug are shown in the last two columns.

Table 2. Frequency of Adverse Events (%)
 | All Adverse Events |  | Possibly – or Probably –; Related Adverse Events
 | Perindopril; n=789 | Placebo; n=223 | Perindopril; n=789 | Placebo; n=223
Cough | 12.0 | 4.5 | 6.0 | 1.8
Back Pain | 5.8 | 3.1 | 0.0 | 0.0
Sinusitis | 5.2 | 3.6 | 0.6 | 0.0
Viral Infection | 3.4 | 1.6 | 0.3 | 0.0
Upper Extremity Pain | 2.8 | 1.4 | 0.2 | 0.0
Hypertonia | 2.7 | 1.4 | 0.2 | 0.0
Dyspepsia | 1.9 | 0.9 | 0.3 | 0.0
Fever | 1.5 | 0.5 | 0.3 | 0.0
Proteinuria | 1.5 | 0.5 | 1.0 | 0.5
Ear Infection | 1.3 | 0.0 | 0.0 | 0.0
Palpitation | 1.1 | 0.0 | 0.9 | 0.0

Of these, cough was the reason for withdrawal in 1.3% of perindopril and 0.4% of placebo patients. While dizziness was not reported more frequently in the perindopril group (8.2%) than in the placebo group (8.5%), it was clearly increased with dose, suggesting a causal relationship with perindopril. Other commonly reported complaints (1% or greater), regardless of causality, include: headache (23.8%), upper respiratory infection (8.6%), asthenia (7.9%), rhinitis (4.8%), low extremity pain (4.7%), diarrhea (4.3%), edema (3.9%), pharyngitis (3.3%), urinary tract infection (2.8%), abdominal pain (2.7%), sleep disorder (2.5%), chest pain (2.4%), injury, paresthesia, nausea, rash (each 2.3%), seasonal allergy, depression (each 2.0%), abnormal ECG (1.8%), ALT increase (1.7%), tinnitus, vomiting (each 1.5%), neck pain, male sexual dysfunction (each 1.4%), triglyceride increase, somnolence (each 1.3%), joint pain, nervousness, myalgia, menstrual disorder (each 1.1%), flatulence and arthritis (each 1.0%), but none of those was more frequent by at least 1% on perindopril than on placebo. Depending on the specific adverse event, approximately 30 to 70% of the common complaints were considered possibly or probably related to treatment.

Stable Coronary Artery Disease

Perindopril has been evaluated for safety in EUROPA, a double-blind, placebo-controlled study in 12,218 patients with stable coronary artery disease. The overall rate of discontinuation was about 22% on drug and placebo. The most common medical reasons for discontinuation that were more frequent on perindopril than placebo were cough, drug intolerance and hypotension.

Below is a list (by body system) of adverse experiences reported in 0.3 to 1% of patients in U.S. placebo-controlled studies in hypertensive patients without regard to attribution to therapy. Less frequent but medically important adverse events are also included; the incidence of these events is given in parentheses.

Body as a Whole: malaise, pain, cold/hot sensation, chills, fluid retention, orthostatic symptoms, anaphylactic reaction, facial edema, angioedema (0.1%).

Gastrointestinal: constipation, dry mouth, dry mucous membrane, appetite increased, gastroenteritis.

Respiratory: posterior nasal drip, bronchitis, rhinorrhea, throat disorder, dyspnea, sneezing, epistaxis, hoarseness, pulmonary fibrosis (<0.1%).

Urogenital: vaginitis, kidney stone, flank pain, urinary frequency, urinary retention.

Cardiovascular: hypotension, ventricular extrasystole, myocardial infarction, vasodilation, syncope, abnormal conduction, heart murmur, orthostatic hypotension.

Endocrine: gout.

Hematology: hematoma, ecchymosis.

Musculoskeletal: arthralgia, myalgia.

CNS: migraine, amnesia, vertigo, cerebral vascular accident (0.2%).

Psychiatric: anxiety, psychosexual disorder.

Dermatology: sweating, skin infection, tinea, pruritus, dry skin, erythema, fever blisters, purpura (0.1%).

Special Senses: conjunctivitis, earache.

Laboratory: potassium decrease, uric acid increase, alkaline phosphatase increase, cholesterol increase, AST increase, creatinine increase, hematuria, glucose increase.

When perindopril erbumine tablets was given concomitantly with thiazide diuretics, adverse events were generally reported at the same rate as those for perindopril erbumine tablets alone, except for a higher incidence of abnormal laboratory findings known to be related to treatment with thiazide diuretics alone (e.g., increases in serum uric acid, triglycerides and cholesterol and decreases in serum potassium).

Potential Adverse Effects Reported with ACE Inhibitors: Other medically important adverse effects reported with other available ACE inhibitors include: cardiac arrest, eosinophilic pneumonitis, neutropenia/agranulocytosis, pancytopenia, anemia (including hemolytic and aplastic), thrombocytopenia, acute renal failure, nephritis, hepatic failure, jaundice (hepatocellular or cholestatic), symptomatic hyponatremia, bullous pemphigoid, pemphigus, acute pancreatitis, falls, psoriasis, exfoliative dermatitis and a syndrome which may include: arthralgia/arthritis, vasculitis, serositis, myalgia, fever, rash or other dermatologic manifestations, a positive ANA, leukocytosis, eosinophilia or an elevated ESR. Many of these adverse effects have also been reported for perindopril.

Fetal/Neonatal Morbidity and Mortality: See WARNINGS: Fetal/Neonatal Morbidity and Mortality.

Clinical Laboratory Test Findings

Hypertension

Hematology, clinical chemistry and urinalysis parameters have been evaluated in U.S. placebo-controlled trials. In general, there were no clinically significant trends in laboratory test findings.

Hyperkalemia: In clinical trials, 1.4% of the patients receiving perindopril erbumine tablets and 2.3% of the patients receiving placebo showed serum potassium levels greater than 5.7 mEq/L. (See PRECAUTIONS.)

BUN/Serum Creatinine Elevations: Elevations, usually transient and minor, of BUN and serum creatinine have been observed. In placebo-controlled clinical trials, the proportion of patients experiencing increases in serum creatinine were similar in the perindopril erbumine tablets and placebo treatment groups. Rapid reduction of long-standing or markedly elevated blood pressure by any anti-hypertensive therapy can result in decreases in the glomerular filtration rate and, in turn, lead to increases in BUN or serum creatinine. (See PRECAUTIONS.)

Hematology: Small decreases in hemoglobin and hematocrit occur frequently in hypertensive patients treated with perindopril erbumine tablets, but are rarely of clinical importance. In controlled clinical trials, no patient was discontinued from therapy due to the development of anemia. Leukopenia (including neutropenia) was observed in 0.1% of patients in U.S. clinical trials (See WARNINGS.)

Liver Function Tests: Elevations in ALT (1.6% perindopril erbumine tablets vs 0.9% placebo) and AST (0.5% perindopril erbumine tablets vs 0.4% placebo) have been observed in U.S placebo-controlled clinical trials. The elevations were generally mild and transient and resolved after discontinuation of therapy.

OVERDOSAGE

In animals, doses of perindopril up to 2,500 mg/kg in mice, 3,000 mg/kg in rats and 1,600 mg/kg in dogs were non-lethal. Past experiences were scant but suggested that overdosage with other ACE inhibitors was also fairly well tolerated by humans. The most likely manifestation is hypotension, and treatment should be symptomatic and supportive. Therapy with the ACE inhibitor should be discontinued, and the patient should be observed. Dehydration, electrolyte imbalance and hypotension should be treated by established procedures.

However, of the reported cases of perindopril overdosage, one (dosage unknown) required assisted ventilation and the other developed hypothermia, circulatory arrest and died following ingestion of up to 180 mg of perindopril. The intervention for perindopril overdose may require vigorous support (see below).

Laboratory determinations of serum levels of perindopril and its metabolites are not widely available, and such determinations have, in any event, no established role in the management of perindopril overdose.

No data are available to suggest physiological maneuvers (e.g., maneuvers to change the pH of the urine) that might accelerate elimination of perindopril and its metabolites. Perindopril can be removed by hemodialysis, with clearance of 52 mL/min for perindopril and 67 mL/min for perindoprilat.

Angiotensin II could presumably serve as a specific antagonist-antidote in the settling of perindopril overdose, but angiotensin II is essentially unavailable outside of scattered research facilities. Because the hypotensive effect of perindopril is achieved through vasodilation and effective hypovolemia, it is reasonable to treat perindopril overdose by infusion of normal saline solution.

DOSAGE AND ADMINISTRATION

Stable Coronary Artery Disease

In patients with stable coronary artery disease, perindopril erbumine tablets should be given at an initial dose of 4 mg once daily for 2 weeks, and then increased as tolerated, to a maintenance dose of 8 mg once daily. In elderly patients (>70 yrs), perindopril erbumine tablets should be given as a 2 mg dose once daily in the first week, followed by 4 mg once daily in the second week and 8 mg once daily for maintenance dose if tolerated.

Hypertension

Use in Uncomplicated Hypertensive Patients: In patients with essential hypertension, the recommended initial dose is 4 mg once a day. The dosage may be titrated upward until blood pressure, when measured just before the next dose, is controlled or to a maximum of 16 mg per day. The usual maintenance dose range is 4 to 8 mg administered as a single daily dose. perindopril erbumine tablets may also be administered in two divided doses. When once-daily dosing was compared to twice-daily dosing in clinical studies, the B.I.D. regimen was generally slightly superior, but not by more than about 0.5 to 1.0 mm Hg.

Use in the Elderly Patients: As in younger patients, the recommended initial daily dosage of perindopril erbumine tablets for the elderly (>65 years) is 4 mg daily, given in one or two divided doses. The daily dosage may be titrated upward until blood pressure, when measured just before the next dose, is controlled, but experience with perindopril erbumine tablets is limited in the elderly at doses exceeding 8 mg. Dosages above 8 mg should be administered with caution and under close medical supervision. (See PRECAUTIONS: Geriatric Use.)

Use in Concomitant Diuretics: If blood pressure is not adequately controlled with perindopril alone, a diuretic may be added. In patients currently being treated with a diuretic, symptomatic hypotension occasionally can occur following the initial dose of perindopril. To reduce likelihood of such reaction, the diuretic should, if possible, be discontinued 2 to 3 days prior to the beginning of perindopril erbumine tablets therapy. (See WARNINGS.) Then, if blood pressure is not controlled with perindopril erbumine tablets alone, the diuretic should be resumed.

If the diuretic cannot be discontinued, an initial dose of 2 to 4 mg daily in one or in two divided doses should be used with careful medical supervision for several hours and until blood pressure has stabilized. The dosage should then be titrated as described above. (See WARNINGS and PRECAUTIONS: Drug Interactions.)

After the first dose of perindopril erbumine tablets, the patient should be followed closely for the first two weeks of treatment and whenever the dose of perindopril erbumine tablets and/or diuretics is increased (See WARNINGS and PRECAUTIONS, Drug Interactions.) In patients who are currently being treated with a diuretic, symptomatic hypotension occasionally can occur following the initial dose of perindopril erbumine tablets. To reduce the likelihood of hypotension, the dose of diuretic, if possible, can be adjusted which may diminish the likelihood of hypotension. The appearance of hypotension after the initial dose of perindopril erbumine tablets does not preclude subsequent careful dose titration with the drug, following effective management of the hypotension.

Dose Adjustment in Renal Impairment

Kinetic data indicate that perindoprilat elimination is decreased in renally impaired patients, with a marked increase in accumulation when creatinine clearance drops below 30 mL/min. In such patients (creatinine clearance <30 mL/min), safety and efficacy of perindopril erbumine tablets have not been established. For patients with lesser degrees of impairment (creatinine clearance above 30 mL/min), the initial dosage should be 2 mg/day and dosage should not exceed 8 mg/day due to limited clinical experience. During dialysis, perindopril is removed with the same clearance as in patients with normal renal function.

HOW SUPPLIED

Perindopril Erbumine Tablets are supplied as below:

2 mg: | White to off-white, round, biconvex tablets, debossed with ‘L’ and ‘U’ on either side of the breakline on one side and ‘C11’ on the other side.; Bottles of 100 NDC 68180-235-01
4 mg: | White to off-white, capsule-shaped, biconvex tablets, debossed with ‘L’ and ‘U’ on either side of the breakline on one side and ‘C12’ on the other side.; Bottles of 100 NDC 68180-236-01
8 mg: | White to off-white, round, biconvex tablets, debossed with ‘L’ and ‘U’ on either side of the breakline on one side and ‘C13’ on the other side.; Bottles of 100 NDC 68180-237-01

Storage Conditions: Store at 20° to 25°C (68° to 77°F) [see USP Controlled Room Temperature]. Protect from moisture.

Keep out of the reach of children.

Manufactured for:
Lupin Pharmaceuticals, Inc.
Baltimore, Maryland 21202
United States

Manufactured by:
Lupin Limited
Goa - 403 722
INDIA

Revision Date: January 2010 Item Code: 21207

PACKAGE/LABEL PRINCIPAL DISPLAY PANEL

NDC 68180-235-01

Perindopril Erbumine Tablets

2 mg

Each tablet contains perindopril erbumine 2 mg.

Rx only

100 Tablets

Dosage and Administration: See accompanying prescribing information.

Keep out of the reach of children.

Store at 20° to 25°C (68° to 77°F) [see USP Controlled Room Temperature]. Protect from moisture.

PACKAGE/LABEL PRINCIPAL DISPLAY PANEL

NDC 68180-236-01

Perindopril Erbumine Tablets

4 mg

Each tablet contains perindopril erbumine 4 mg.

Rx only

100 Tablets

Dosage and Administration: See accompanying prescribing information.

Keep out of the reach of children.

Store at 20° to 25°C (68° to 77°F) [see USP Controlled Room Temperature]. Protect from moisture.

PACKAGE/LABEL PRINCIPAL DISPLAY PANEL

NDC 68180-237-01

Perindopril Erbumine Tablets

8 mg

Each tablet contains perindopril erbumine 8 mg.

Rx only

100 Tablets

Dosage and Administration: See accompanying prescribing information.

Keep out of the reach of children.

Store at 20° to 25°C (68° to 77°F) [see USP Controlled Room Temperature]. Protect from moisture.